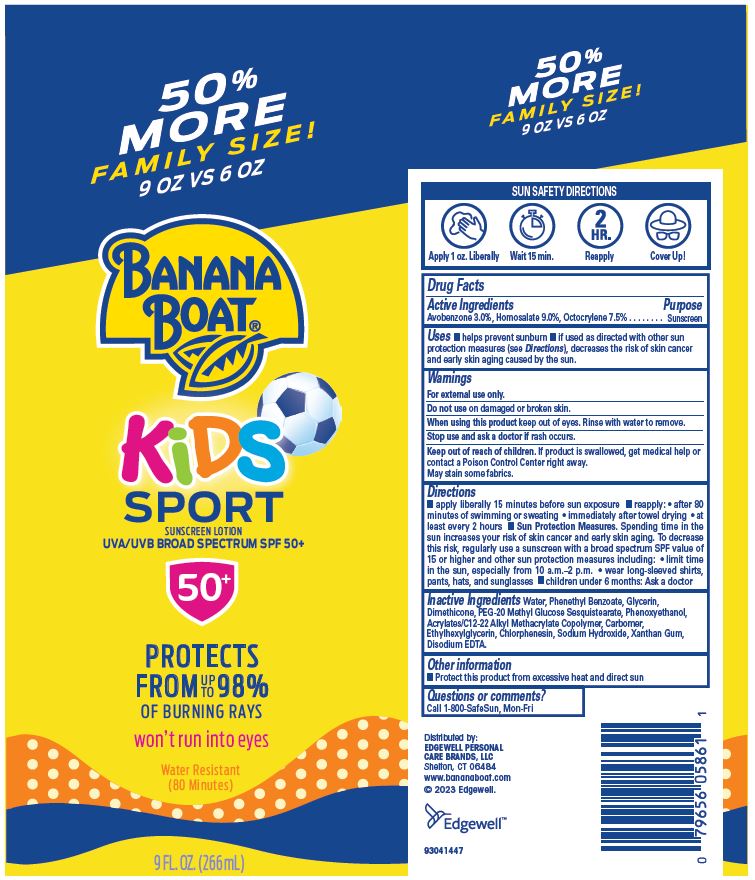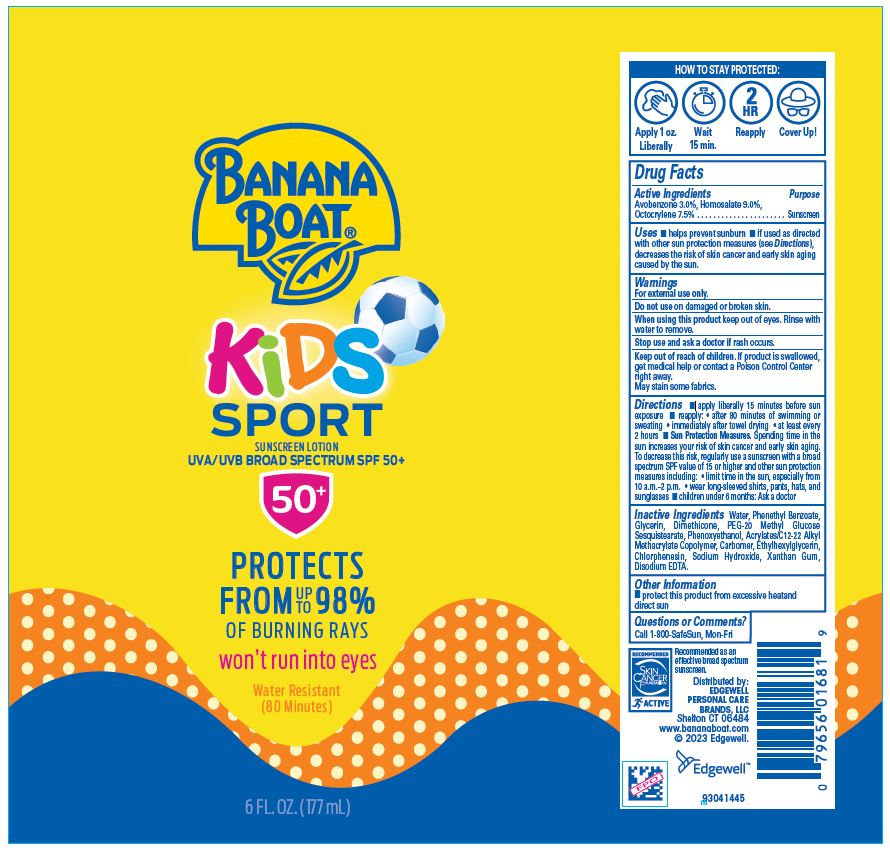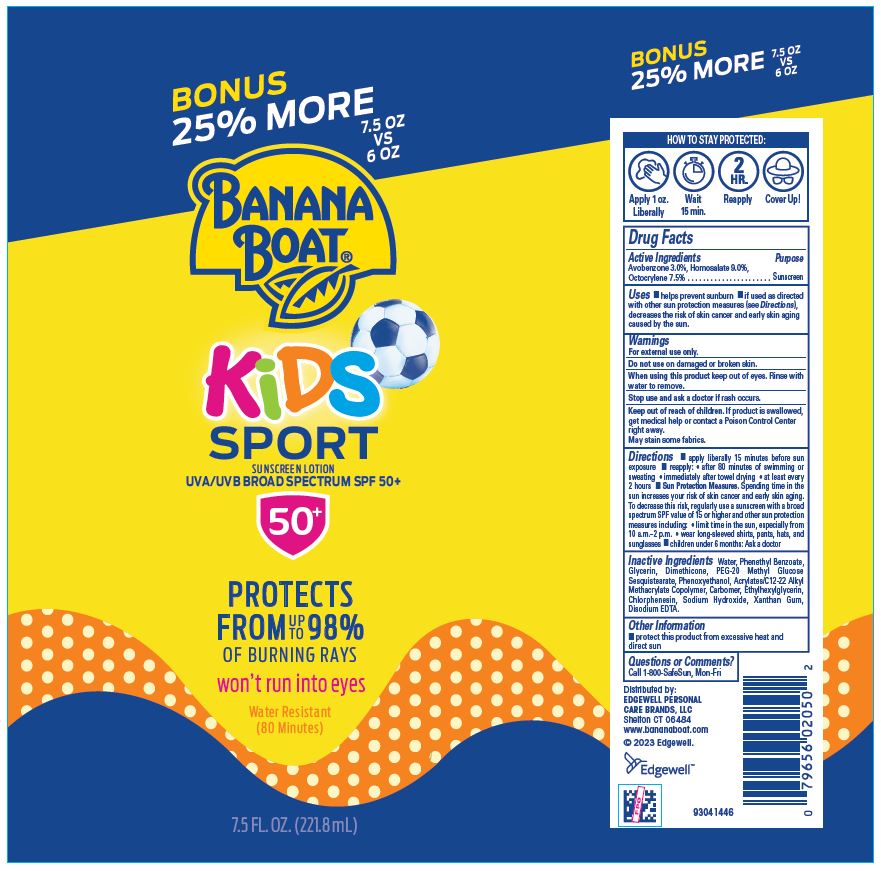 DRUG LABEL: BANANA BOAT
NDC: 63354-081 | Form: LOTION
Manufacturer: Edgewell Personal Care Brands LLC
Category: otc | Type: HUMAN OTC DRUG LABEL
Date: 20250817

ACTIVE INGREDIENTS: OCTOCRYLENE 7.5 g/100 g; AVOBENZONE 3 g/100 g; HOMOSALATE 9 g/100 g
INACTIVE INGREDIENTS: WATER; PHENETHYL BENZOATE; CARBOMER HOMOPOLYMER, UNSPECIFIED TYPE; XANTHAN GUM; SODIUM HYDROXIDE; ETHYLHEXYLGLYCERIN; CHLORPHENESIN; GLYCERIN; DIMETHICONE; PEG-20 METHYL GLUCOSE SESQUISTEARATE; PHENOXYETHANOL; EDETATE DISODIUM

Active Ingredients

Avobenzone 3.0%, Homosalate 9.0%, Octocrylene 7.5%

Purpose

Sunscreen

Uses

• helps prevent sunburn • if used as directed with other sun protection measures (see Directions), decreases the risk of skin cancer and early skin aging caused by the sun.

Warnings

For external use only.

May stain some fabrics.

Do not use

on damaged or broken skin.

When using this product

keep out of eyes. Rinse with water to remove.

Stop use and ask a doctor if

rash occurs.

Keep out of reach of children.

If product is swallowed, get medical help or contact a Poison Control Center right away.

Directions

• apply liberally 15 minutes before sun exposure • reapply: • after 80 minutes of swimming or sweating • immediately after towel drying • at least every 2 hours • Sun Protection Measures. Spending time in the sun increases your risk of skin cancer and early skin aging. To decrease this risk, regularly use a sunscreen with a broad spectrum SPF value of 15 or higher and other sun protection measures including: • limit time in the sun, especially from 10 a.m.–2 p.m. • wear long-sleeved shirts, pants, hats, and sunglasses • children under 6 months: Ask a doctor

Inactive Ingredients

Water, Phenethyl Benzoate, Glycerin, Dimethicone, PEG-20 Methyl Glucose Sesquistearate, Phenoxyethanol, Acrylates/C12-22 Alkyl Methacrylate Copolymer, Carbomer, Ethylhexylglycerin, Chlorphenesin, Sodium Hydroxide, Xanthan Gum, Disodium EDTA.

Other Information

• protect this product from excessive heat and direct sun

Questions or Comments?

Call 1-800-SafeSun, Mon-Fri

PACKAGE LABEL

BANANA
BOAT®
KiDS
SPORT
SUNSCREEN LOTION
UVA/UVB BROAD SPECTRUM SPF 50+
50+
PROTECTS
FROM 98%
OF BURNING RAYS
won’t run into eyes
Water Resistant
(80 Minutes)
6 FL. OZ. (177 mL)

BONUS
25% MORE
7.5 OZ
VS
6 OZ
BANANA
BOAT®
KiDS
SPORT
SUNSCREEN LOTION
UVA/UVB BROAD SPECTRUM SPF 50+
50+
PROTECTS
FROM 98%
OF BURNING RAYS
won’t run into eyes
Water Resistant
(80 Minutes)
7.5 FL. OZ. (221.8 mL)

50% MORE
FAMILY SIZE!
9 OZ VS 6 OZ
BANANA
BOAT®
KiDS
SPORT
SUNSCREEN LOTION
UVA/UVB BROAD SPECTRUM SPF 50+
50+
PROTECTS
FROM 98%
OF BURNING RAYS
won’t run into eyes
Water Resistant
(80 Minutes)
9 FL. OZ. (266 mL)